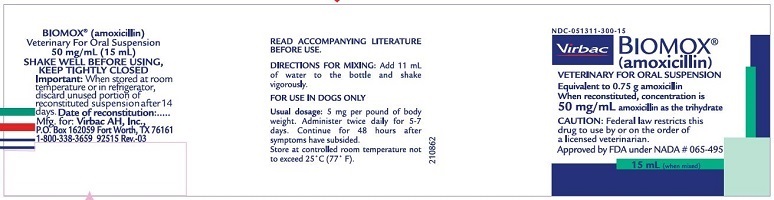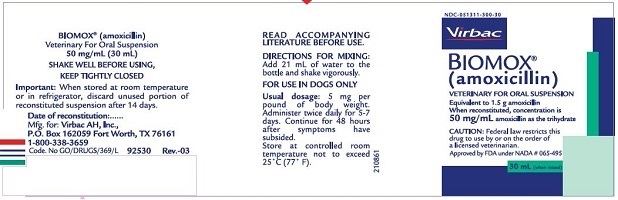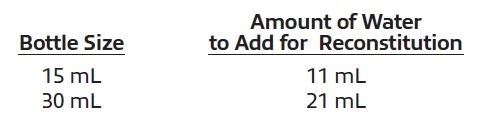 DRUG LABEL: Biomox
NDC: 51311-300 | Form: SUSPENSION
Manufacturer: Virbac AH, Inc.
Category: animal | Type: PRESCRIPTION ANIMAL DRUG LABEL
Date: 20220105

ACTIVE INGREDIENTS: amoxicillin 0.75 g/15 mL

Approved by FDA under NADA # 065-495
BIOMOX®
(amoxicillin)

Veterinary For Oral Suspension
For use in DOGS only.

DESCRIPTION

BIOMOX® (amoxicillin) is a broad-spectrum, semisynthetic antibiotic which provides bactericidal activity against a wide range of common gram-positive and gram-negative pathogens. Amoxicillin chemically is D-(-)α-amino-p-hydroxybenzyl penicillin trihydrate.

Inactive Ingredients

Cherry Flavor, Silicon Dioxide NF, FD&C Red #40, Polyoxyethylene-Polyoxypropylene Glycol, Sodium Benozate, Sodium Citrate, Sodium Saccharin, and Sucrose

ACTION

Amoxicillin has bactericidal activity against susceptible organisms similar to that of ampicillin. It acts by inhibiting the biosynthesis of bacterial
wall mucopeptides. Most strains of the following gram-positive and gramnegative bacteria have demonstrated susceptibility to: amoxicillin, both in vitro and in vivo: nonpenicillinase-producing staphylococci, alpha- and betahemolytic streptococci, Streptococcus faecalis, Escherichia coli and Proteus mirabilis. Amoxicillin does not resist destruction by penicillinase; therefore, it is not effective against penicillinase-producing bacteria, particularly resistant staphylococci. Most strains of Enterobacter and klebsiella and all strains of Pseudomonas are resistant.

Amoxicillin may be given without regard to meals because it is stable in gastric acid. It is rapidly absorbed following oral administration and diffuses readily into most body fluids and tissues. It diffuses poorly into the brain and spinal fluid except when the meninges are inflamed. Most of the amoxicillin is excreted in the urine unchanged.

INDICATIONS

BIOMOX® (amoxicillin) for oral suspension is indicated in the treatment of the following infections in dogs when caused by susceptible strains of organisms:

BACTERIAL DERMATITIS due to Staphylococcus aureus, Streptococcus spp.; Staphylococcus spp.; and E. coli.

SOFT TISSUE INFECTIONS (abscesses, wounds, lacerations) due to Staphylococcus aureus, Streptococcus spp.; E. coli, Proteus mirabilis and
Staphylococcus spp.

As is true with all antibiotic therapy, appropriate in vitro cultures and sensitivities should be conducted prior to treatment.

CONTRAINDICATIONS

Use of amoxicillin is contraindicated in animals with a history of an allergic reaction to penicillin.

ADVERSE REACTIONS

Amoxicillin is a semisynthetic penicillin and, therefore, has the potential for producing allergic reactions. Epinephrine and/or steroids should be administered if an allergic reaction occurs.

WARNINGS

For use in dogs only.

PRECAUTIONS

Until adequate reproductive studies are accomplished, Biomox (amoxicillin) for oral suspension should not be used in pregnant or breeding
animals.

CAUTION

Federal law restricts this drug to use by or on the order of a licensed veterinarian.

DOSAGE AND ADMINISTRATION

The recommended dosage is 5 mg per pound of body weight administered twice daily for 5 to 7 days. Continue for 48 hours after all symptoms have subsided. If no improvment is noted in 5 days, the diagnosis should be reconsidered and therapy changed.

DIRECTIONS FOR MIXING ORAL SUSPENSION

Add sufficient water to the bottle as indicated in the table below and shake vigorously. Each mL of suspension will contain 50 mg of amoxicillin as the trihydrate.

Note: When stored at room temperature or in refrigerator, discard unused portion of reconstituted suspension after 14 days.

SUPPLY

Bimox® (amoxicillin) for oral suspension is supplied in bottles containing 0.75 g of amoxicillin activity in bottles of 15 mL or 1.5 g of amoxicillin
activity in bottles of 30 mL. After reconstitution with the required amount of water, each mL will contain 50 mg of amoxicillin as the trihydrate.

Manufactured for:
Virbac AH, Inc.
P.O. Box 162059
Fort Worth, TX 76161
1-800-338-3659

92515 07/19 Rev.-03